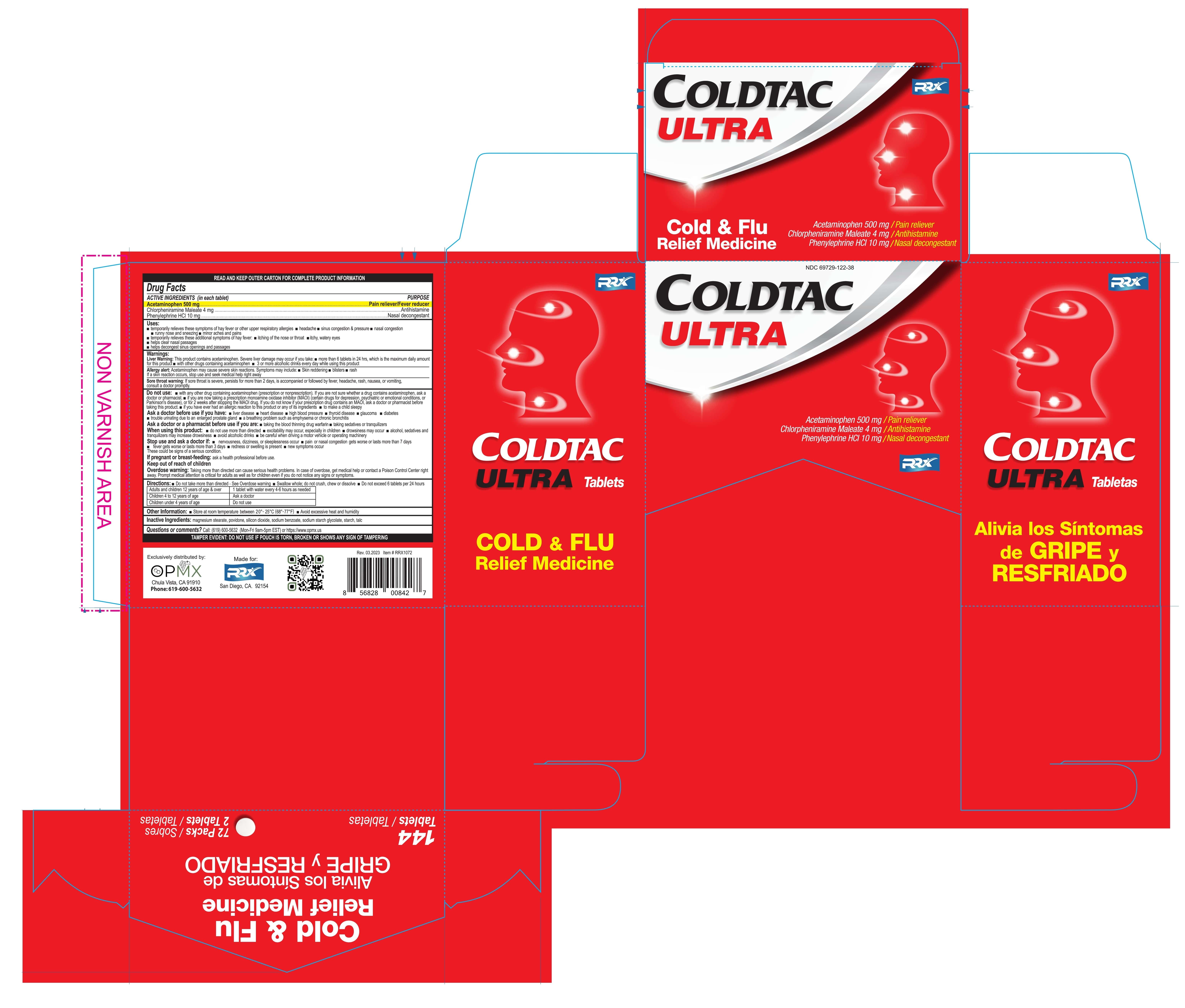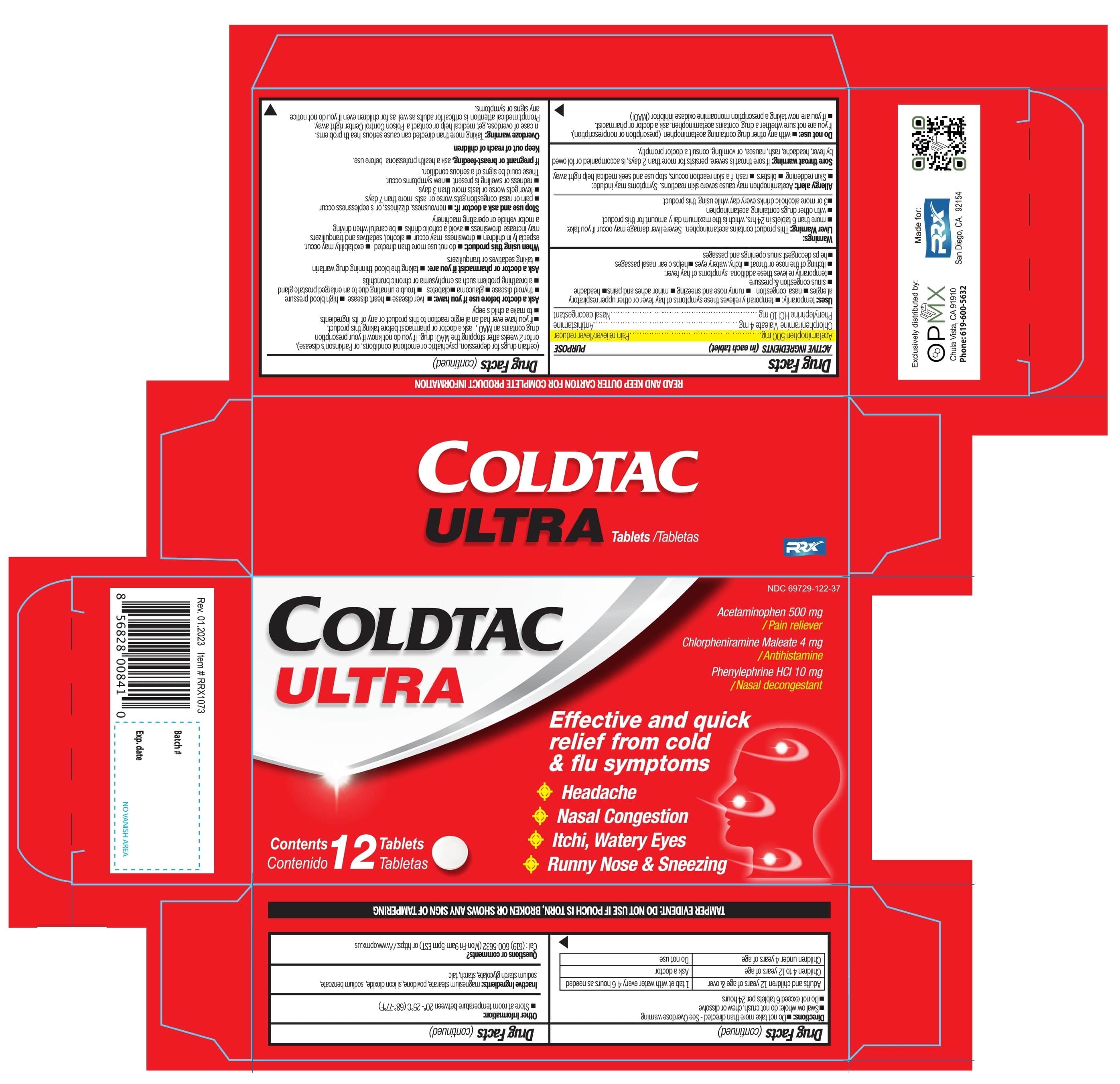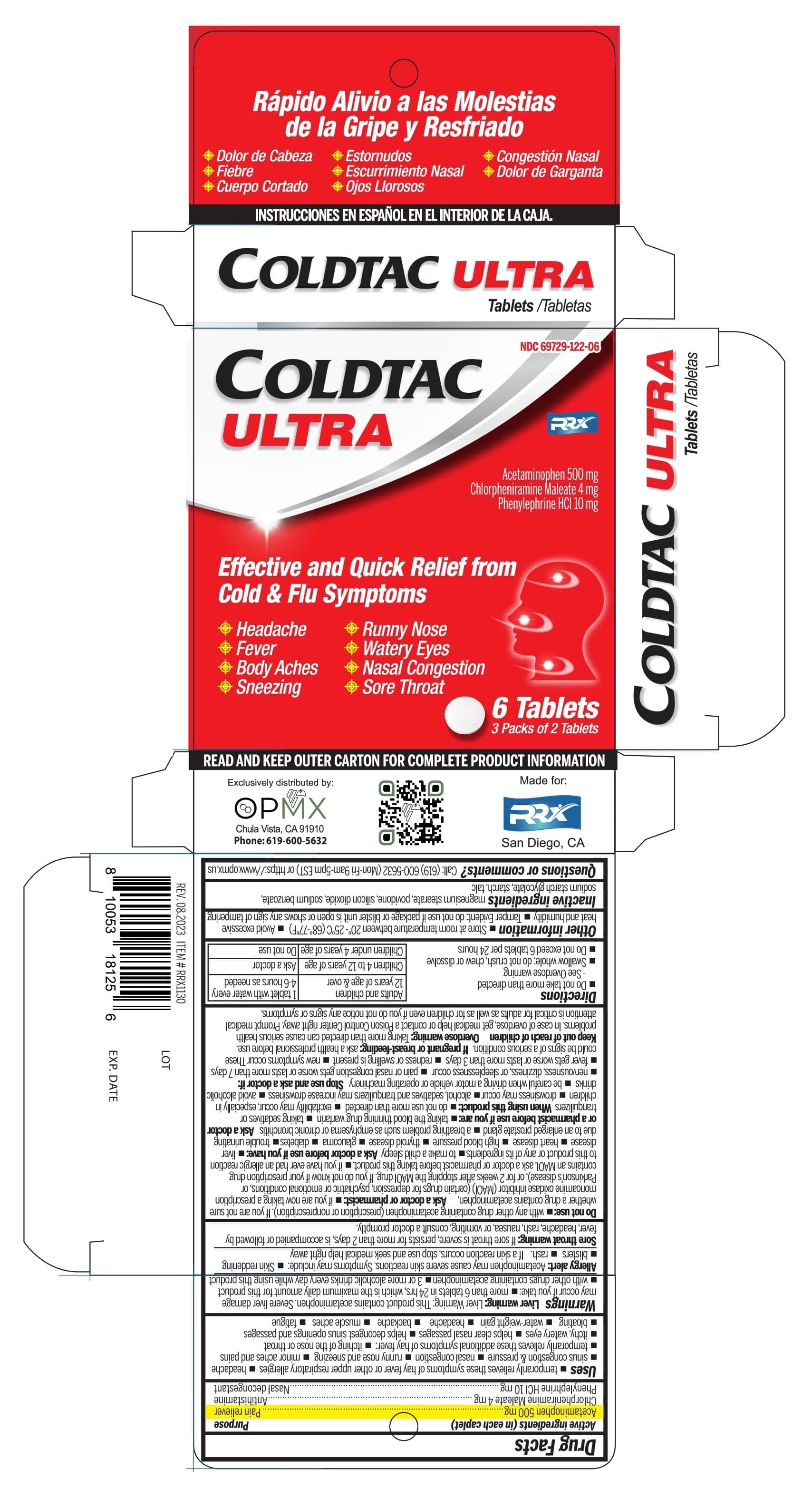 DRUG LABEL: Acetaminophen, Chlorpheniramine Maleate, Phenylephrine HCl
NDC: 69729-122 | Form: TABLET
Manufacturer: OPMX LLC
Category: otc | Type: HUMAN OTC DRUG LABEL
Date: 20241203

ACTIVE INGREDIENTS: ACETAMINOPHEN 500 mg/1 1; CHLORPHENIRAMINE MALEATE 4 mg/1 1; PHENYLEPHRINE HYDROCHLORIDE 10 mg/1 1
INACTIVE INGREDIENTS: SODIUM BENZOATE; SODIUM STARCH GLYCOLATE TYPE A POTATO; TALC; SILICON DIOXIDE; MAGNESIUM STEARATE; STARCH, CORN; POVIDONE K30

Coldtac Ultra tabs
(Acetaminophen 500mg, Chlorpheniramine Maleate 4mg, Phenylephrine HCl 10mg Tablet)

Active ingredients

Purpose

Active ingredients (in each caplet) | Purpose
Acetaminophen 500 mg | Pain reliever
Chlorpheniramine Maleate 4 mg | Antihistamine
Phenylephrine HCl 10 mg | Nasal decongestant

Uses

Temporarily relieves these symptoms of hay fever or other respiratory allergies:

- headache
- nasal congestion
- sinus congestion & pressure
- runny nose and sneezing
- minor aches & pain

Temporarily relieves these additional symptoms of hay fever:

- itching of the nose or throat
- itchy, watery eyes
- helps clear nasal passages
- helps decongest sinus opening and passages

Warnings

Liver warning:

This product contains acetaminophen. Severe liver damage may occur if you take :

- more than 6 tablets in 24 hours, which is the maximum daily amount for this product
- with other drugs contains acetaminophen
- 3 or more alcoholic drinks every day while using this product.

Allergy alert:

Acetaminophen may cause severe skin reactions. Symptoms may include:

- skin reddening
- blisters
- rash

If a skin reaction occurs, stop use and seek medical help right away.

Sore throat warning:

if sore throat is severe, persists for more than 2 days, is accompanied or followed by fever, headache, rash, nausea, or vomiting, consult doctor promptly

Do not use

- with any other drug containing acetaminophen (prescription or nonprescription). If you are not sure whether a drug contains acetaminophen,
- If you are not sure whether a drug contains acetaminophen, ask a doctor or pharmacist
  If you are now taking a prescription monoamine oxidase inhibitor (MAOI) (certain drugs for depression, psychiatric, or emotional conditions, or Parkinson’s disease), or for 2 weeks after stopping the MAOI drug. If you do not know if your prescription drug contains an MAOI
- if you have ever had an allergic reaction to this product or any of its ingredients.
- to make a child sleepy

Ask a doctor before use if you have:

- liver disease
- heart disease
- high blood pressure
- thyroid disease
- glaucoma
- diabetes
- trouble urinating due to enlarged prostate gland
- a breathing problem such as emphysema or chronic bronchitis

Ask a doctor ot pharmacist if you are:

- taking the blood thinning drug warfarin
- taking sedatives or tranquilizers

When using this product:

- do not use more than directed
- excitability may occur, especially in children
- drowsiness may occur
- alcohol, sedatives and tranquilizers may increase drowsiness
- avoid alcohol drinks
- be careful when driving a motor vehicle or operating machinery

Stop use and ask a doctor if:

- nervousness, dizziness, or sleeplessness occur
- pain, nasal congestion, or cough gets worse or lasts more than 7 days
- fever gets worse or last more than 3 days
- redness or swelling is present
- new symptoms occur

These could be signs of a serious condition.

If pregnant or breast-feeding,

ask a health professional before use.

Keep out of reach of children.

Overdose warning

Taking more than directed can cause serious health problems. In case of overdose, get medical help or contact a Poison Control Center right away. Prompt medical attention is critical for adults as well as for children even if you do not notice any signs or symptoms.

Directions

- Do not take more than directed - See overdose warning
- Swallow whole; do not crush, chew or dissolve
- Do not exceed 6 tablets per 24 hours

Adults and children 12 years of age & over | 1 tablet with water every 4-6 hours as needed
Children 4 to 12 years of age | Ask a doctor
Children under 4 years of age | Do not use

Other information

- Store at room temperature between 20-25°C (68-77ºF)
- Tamper evident: Do not use if pouch is torn, broken or shows any sing of tampering

Inactive ingredients

magnesium stearate, povidone, silicon dioxide, sodium benzoate, sodium starch glycolate, starch, talc

Questions or comments?

Call: (619) 600-5632 (Mon-Fri 9am-5pm EST) or https://www.opmx.us

Coldtac Ultra

NDC 69729-122-06

NDC 69729-122-37

NDC 69729-122-38